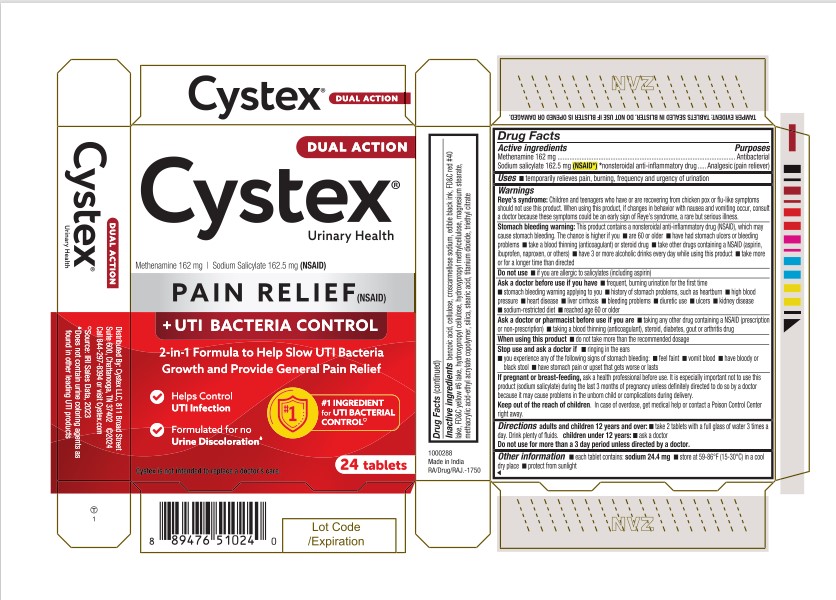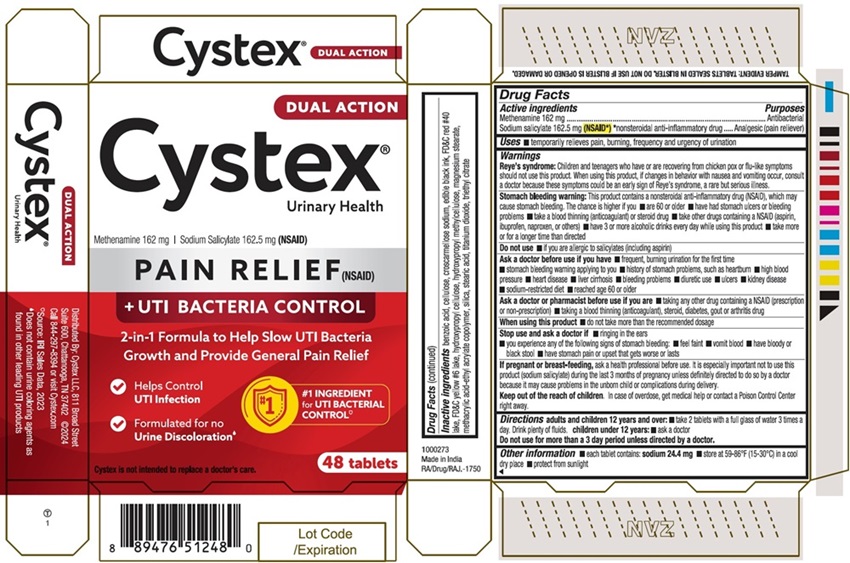 DRUG LABEL: Cystex
NDC: 69693-518 | Form: TABLET
Manufacturer: Clarion Brands, LLC
Category: otc | Type: HUMAN OTC DRUG LABEL
Date: 20251226

ACTIVE INGREDIENTS: METHENAMINE 162 mg/1 1; SODIUM SALICYLATE 162.5 mg/1 1
INACTIVE INGREDIENTS: BENZOIC ACID; POWDERED CELLULOSE; CROSCARMELLOSE SODIUM; FD&C RED NO. 40; FD&C YELLOW NO. 6; HYDROXYPROPYL CELLULOSE, UNSPECIFIED; HYPROMELLOSE, UNSPECIFIED; MAGNESIUM STEARATE; METHACRYLIC ACID AND ETHYL ACRYLATE COPOLYMER; SILICON DIOXIDE; STEARIC ACID; TITANIUM DIOXIDE; TRIETHYL CITRATE

Drug Facts

Active Ingredients

Methenamine 162 mg

Antibacterial

Sodium Salicylate 162.5 mg (NSAID*) *nonsteroidal anti-inflammatory drug.....Analgesic (pain reliever)

Purposes

Antibacterial

Uses

temporarily relieves pain, burning, frequency and urgency of urination

Warnings

Reye's syndrome:Children and teenagers who have or are recovering from chicken pox or flu-like symptoms should not use this product. When using this product, if changes in behavior with nausea and vomiting occur, consult a doctor because these symptoms could be an early sign of Reye's syndrome, a rare but serious illness.

Stomach bleeding warning:This product contains a nonsteroidal anti-inflammatory drug (NSAID), which may cause stomach bleeding. The chance is higher if you

- are 60 or older
- have stomach ulcers or bleeding problems
- take a blood thinning (anticoagulant) or steroid drug
- take other drugs containing an NSAID (aspirin, ibuprofen, naproxen, or others)
- have 3 or more alcoholic drinks every day while using this product
- take more or for a longer time than directed

Do not use

- if you are allergic to salicylates (including aspirin)

Ask a doctor before use if you are

- frequent, burning urination for the first time
- the stomach bleeding warning applying to you
- history of stomach problems, such as heartburn
- high blood pressure
- heart disease
- liver cirrhosis
- bleeding problems
- diuretic use
- ulcers
- kidney disease
- a sodium restricted diet
- reach age 60 or older

Ask a doctor or pharmacist before use if you are

- taking any other drug containing an NSAID (prescription or non-prescription)
- taking a blood thinning (anticoagulant), steroid, diabetes, gout or arthritis drug

When using this product

- do not take more than the recommended dosage

Stop use and ask a doctor if

- ringing in the ears
- you experience any of the following signs of stomach bleeding:
  - feel faint
  - vomit blood
  - have bloody or black stools
  - have stomach pain or upset that gets worse or lasts

PREGNANCY OR BREAST FEEDING

If pregnant or breast feeding ask a health professional before use. It is especially important not to use this product (sodium salicylate) during the last 3 months of pregnancy unless definitely directed to do so by a doctor because it may cause problems in the unborn child or complications during delivery.

KEEP OUT OF REACH OF CHILDREN

Keep out of the reach of children.In case of overdose, get medical help or contact a Poison Control Center right away.

Directions

Adults and children 12 years and over:

- take 2 tablets with a full glass of water 3 times a day. Drink plenty of fluids.

Children under 12 years:

- ask a doctor.

Do not use for more than a 3 day period unless directed by a doctor.

Other information

- each tablet contains: sodium 24.4 mg
- store at 59-86°F (15-30°C) in a cool dry place
- protect from sunlight

Inactive ingredients

benzoic acid, cellulose, croscarmellose sodium, edible black ink, fd&c red #40 lake, fd&c yellow #6 lake, hydroxypropyl cellulose, hydroxypropyl methylcellulose, magnesium Stearate, methacrylic acid-ethyl acrylate copolymer, silica, stearic acid, titanium dioxide, Triethyl citrate

PRINCIPAL DISPLAY PANEL

DUAL ACTION
Cystex ®
Urinary Health
Methenamine 162 mg | Sodium Salicylate 162.5 mg (NSAID)
PAIN RELIEF (NSAID)
+ UTI BACTERIA CONTROL
2-in-1 Formula to Help Slow UTI Bacteria
Growth and Provice General Pain Relief
Helps Control
UTI infection
Formulated for no
Urine Discoloration
#1 Ingredient for UTI BACTERIAL
Control*
Cystex is not intended to replace a doctor's care.
24 Tablets
TAMPER EVIDENT: TABLETS SEALED IN BLISTER. DO NOT USE IF BLISTER IS OPENED OR DAMAGED.
Distributed by: Cystex, LLC 811 Broad Street
Suite 600, Chattanooga, TN 37402 ©2024
Call 844-297-8394 or visit Cystex.com
*Source: IRI Sales Data, 2023.
Does not contain urine coloring agents as
found in other leading UTI products
1000288
Made In India
RA/Drug/RAJ.-1750

48 tablets
1000273